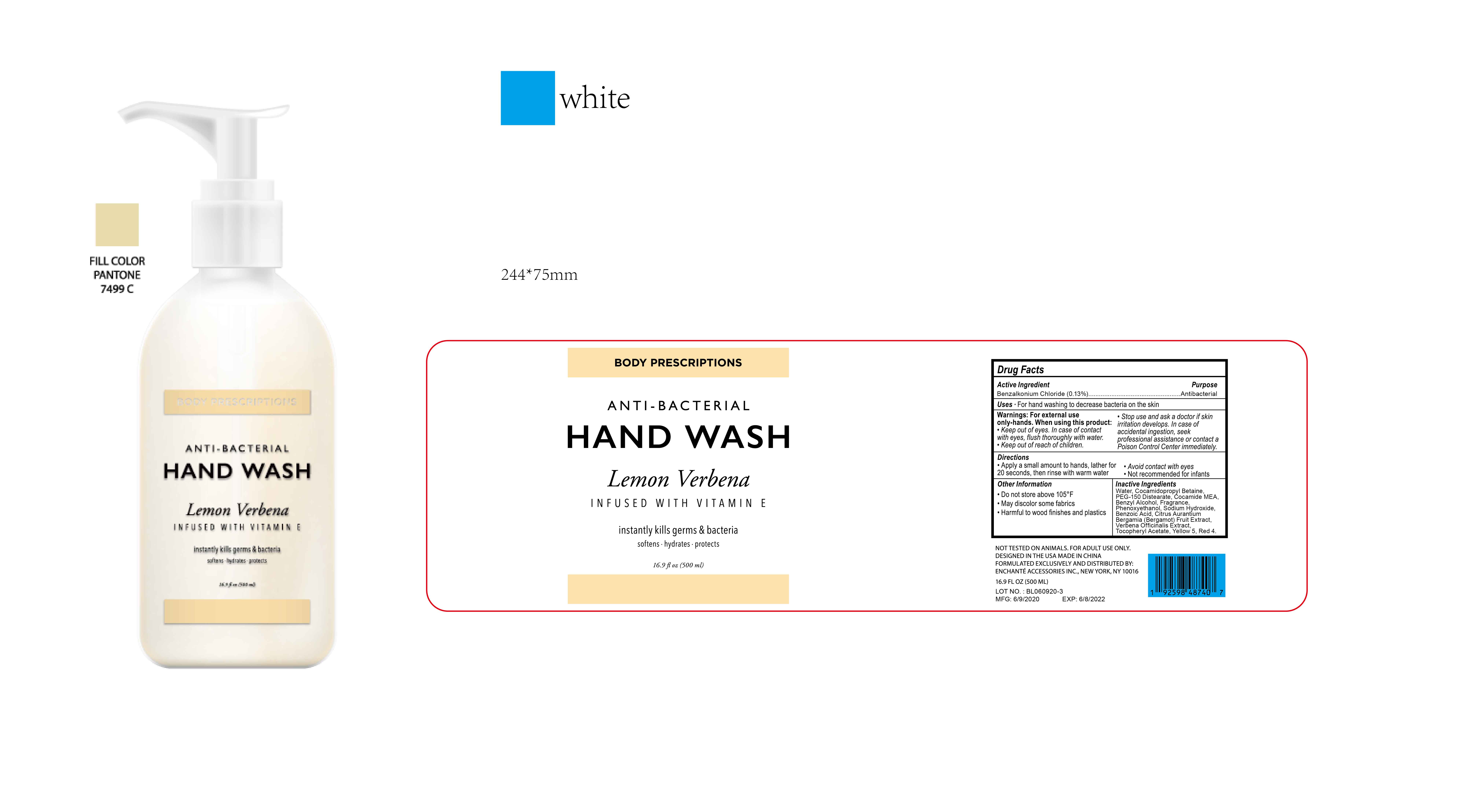 DRUG LABEL: BODY PRESCRIPTIONS ANTIBACTERIAL HAND WASH Lemon Verbena
NDC: 50563-237 | Form: SOLUTION
Manufacturer: ENCHANTE ACCESSORIES INC.
Category: otc | Type: HUMAN OTC DRUG LABEL
Date: 20200630

ACTIVE INGREDIENTS: BENZALKONIUM CHLORIDE 0.13 g/100 mL
INACTIVE INGREDIENTS: COCAMIDOPROPYL BETAINE; PEG-150 DISTEARATE; BENZYL ALCOHOL; PHENOXYETHANOL; WATER; SODIUM HYDROXIDE; BENZOIC ACID; .ALPHA.-TOCOPHEROL ACETATE; VERBENA OFFICINALIS; FD&C RED NO. 4; FD&C YELLOW NO. 5

G0ABHW07

Active Ingredient

Benzalkonium Chloride 0.13%

Purpose

Antibacterial

Use

■ For hand washing to decrease bacteria on hands

WARNINGS

For external use only - hands

When Using this Product

Keep out of eyes. In case of contact with eyes, flush thoroughly with water

Stop use and ask a doctor if skin irritation develops.

Keep out of reach of children. In case of accidental ingestion, seek professional assistance or contact a poison control center immediately

Directions

Apply a small amount to hands. Lather for at least 20 seconds then rinse with warm water

Avoid contact with eyes

Not recommended for infants

Other Information

Do not store above 105F

May discolor some fabrics

Harmful to wood finishes and plastics

Inactive ingredients

Water, Cocamidopropyl Betaine, PEG-150 Distearate, Cocamide MEA, Benzyl Alcohol, Fragrance, Phenoxyethanol, Sodium
Hydroxide, Tocopheryl Acetate, Benzoic Acid, Citrus Aurantium Bergamia (Bergamot) Fruit Extract, Verbena Officinalis Extract, Yellow 5, Red 4